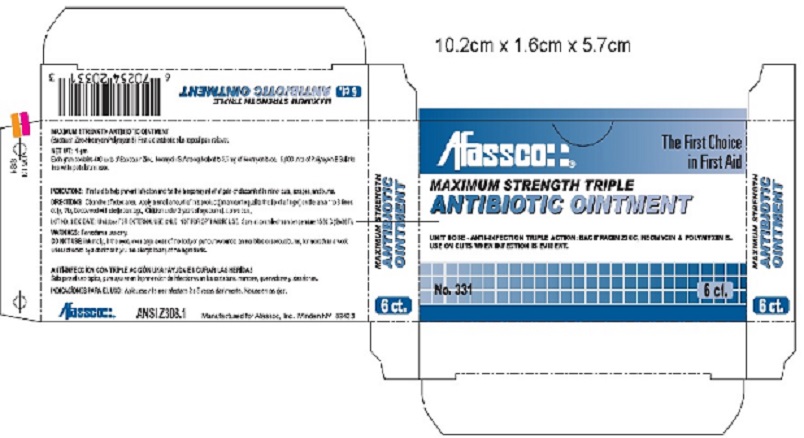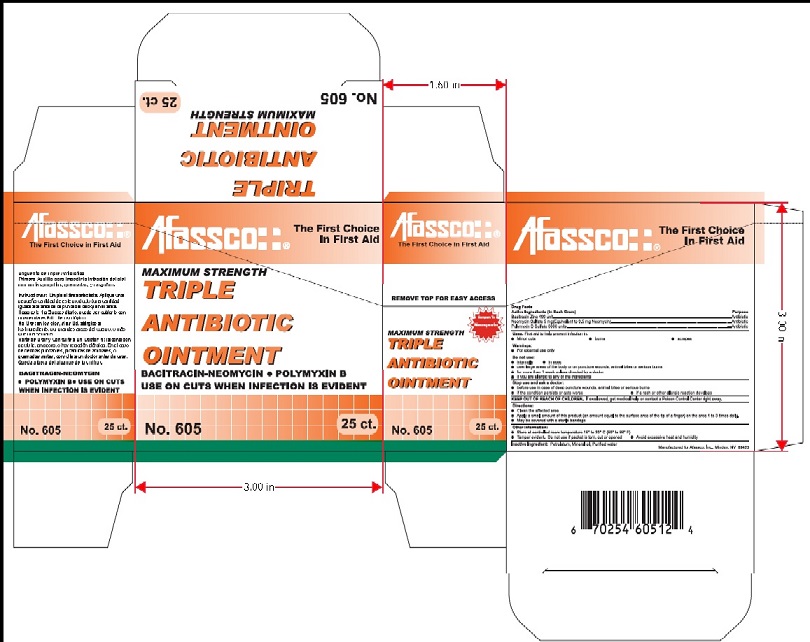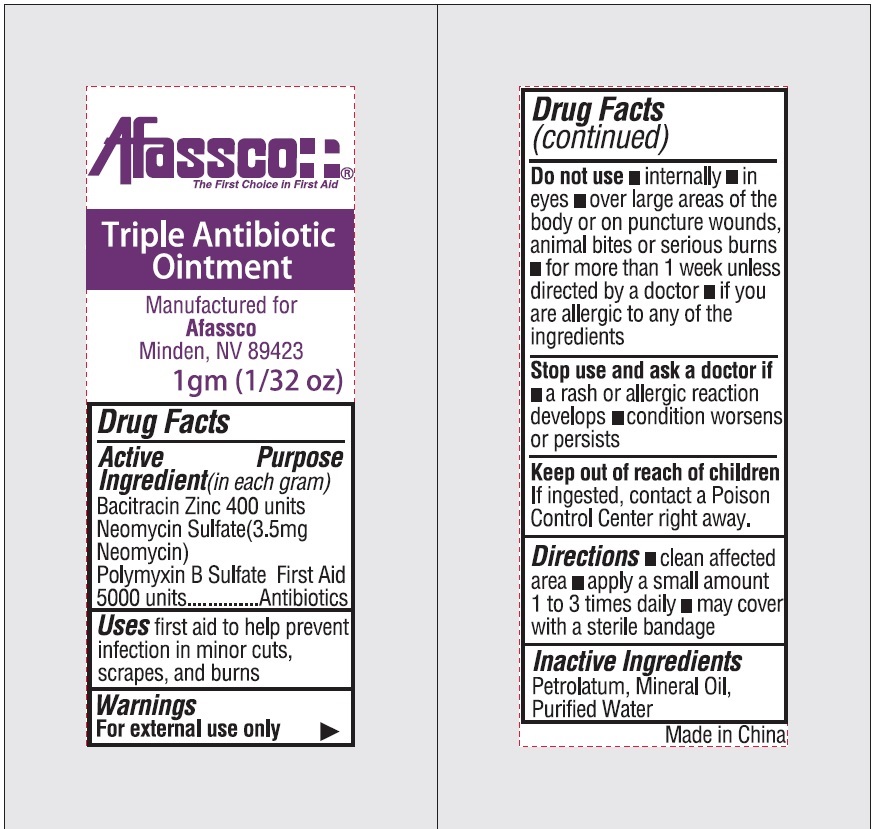 DRUG LABEL: Afassco Triple Antibiotic
NDC: 51532-4605 | Form: OINTMENT
Manufacturer: Afassco Inc.
Category: otc | Type: HUMAN OTC DRUG LABEL
Date: 20230112

ACTIVE INGREDIENTS: BACITRACIN ZINC 400 [iU]/1 g; NEOMYCIN SULFATE 3.5 mg/1 g; POLYMYXIN B SULFATE 5000 [iU]/1 g
INACTIVE INGREDIENTS: PETROLATUM; MINERAL OIL; WATER

Afassco Triple Antibiotic Ointment

Drug Facts

Active Ingredient (in each gram)

Bacitracin Zinc 400 units

Neomycin Sulfate (3.5mg Neomycin)

Polymyxin B Sulfate 5000 units

Purpose

First Aid Antibiotics

INDICATIONS AND USAGE

Uses first aid to help prevent

infection in minor cuts,

scrapes, and burns.

Warnings

For external use only

Do not use ■ internally ■ in

eyes ■ over large areas of

the body or on puncture wounds,

animal bites or serious burns

■ for more than 1 week unless

directed by a doctor ■ if you

are allergic to any of the

ingredients

Stop use and ask a doctor if

■ a rash or allergic reaction

develops ■ condition worsens

or persists

Keep out of reach of children

If ingested, contact a Poison

Control Center right away.

DOSAGE AND ADMINISTRATION

Directions ■ clean affected

area ■ apply a small amount

1 to 3 times daily ■ may cover

with a sterile bandage

Inactive Ingredients

Petrolatum, Mineral Oil,

Purified Water

Principal Display Panel

Afassco¦ ¦®

The First Choice

in First Aid

MAXIMUM STRENGTH TRIPLE

ANTIBIOTIC OINTMENT

UNIT DOSE - ANTI-INFECTION TRIPLE ACTION: BACITRACIN ZINC, NEOMYCIN & POLYMYXIN B.

USE ON CUTS WHEN INFECTION IS EVIDENT.

No. 331 6 ct.

MAXIMUM STRENGTH TRIPLE

ANTIBIOTIC OINTMENT

6 ct.

MAXIMUM STRENGTH TRIPLE

ANTIBIOTIC OINTMENT

6 ct.

MAXIMUM STRENGTH ANTIBIOTIC OINTMENT

(Bacitracin Zinc-Neomycin-Polymyxin B) First aid antibiotic plus topical pain reliever.

NET WT. 1 gmEach gram contains 400 units of Bacitracin Zinc, Neomycin Sulfate equivalent to 3.5 mg of Neomycin base, 5000 units of Polymyxin B Sulfate

in a white pertroleum base.

INDICATIONS: First aid to help prevent infection and for the temporary relief of pain or discomfort i minor cuts, scrapes and burns.

DIRECTIONS: Clean the affected area. Apply a small amount of this product (an amount equal to the tip of a finger) on on the area 1 to 3

daily. May be covered with sterile bandage. Children under 2 years of age consult a physician.

LOT NO. & EXP DATE: Unit dose FOR EXTERNAL USE ONLY. NOT FOR OPTHALMIC USE. Store at controlled room temperature 15-30 C (59-86 F).

WARNINGS: For external use only.

DO NOT USE: Internally, in the eyes, over large aeas of the body or puncture wounds, animal bites or serious burns, for more than a week

unless directed by a doctor or if you are allergic to any of the ingredients.

ANTI-INFECCION CON TRIPLE ACCION UNA / AYUDA EN CURRAR LAS HERIDAS

Solo para el uso topico, para ayudar en la prevencion de infecciones en las cortaduras menoras, quemadoras y abrasiones.

INDICACIONES PARA EL USO: Apliquese a la area afectada 2 a 5 veces diariamente. No use en los ojos.

Afassco¦ ¦® ANZI Z308.1 Manufactured for Afassco, Inc., Minden, NV 89423

6 ct,

MAXIMUM STRENGTH TRIPLE

ANTIBIOTIC OINTMENT

6 70254 20331 3

↓Principal Display 6 ct. Package↓

↓25 ct. Package↓

↓Unit Dose Package↓

Afassco¦ ¦®

The First Choice in First Aid

Triple Antibiotic Ointment

Manufactured for

Afassco

Minden, NV 89423

1 gm (1/32 oz)

Made in China

Triple Antibiotic Ointment by Afassco

res